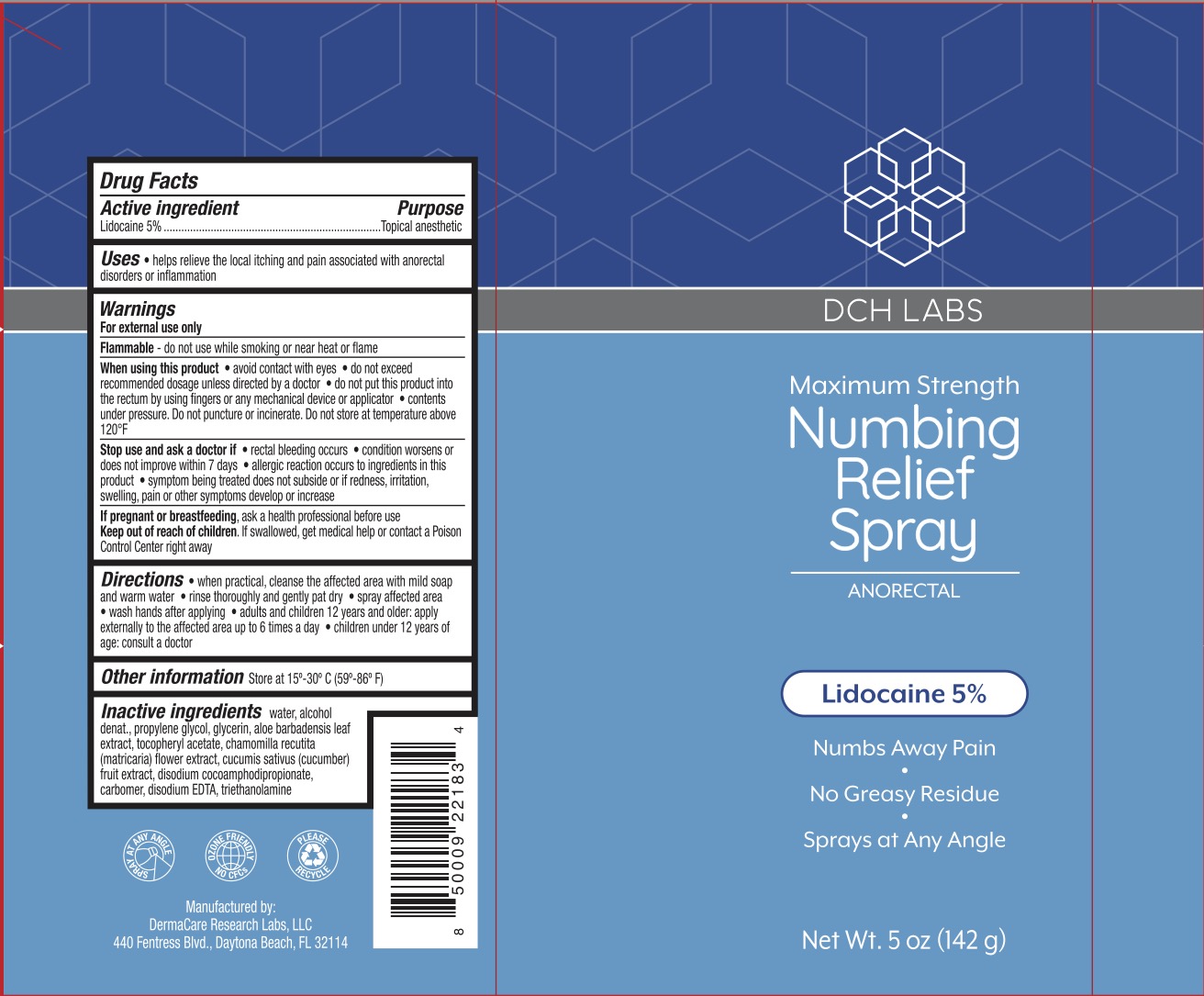 DRUG LABEL: DCH Numbing Relief
NDC: 72839-173 | Form: SPRAY
Manufacturer: Derma Care Research Labs, LLC
Category: otc | Type: HUMAN OTC DRUG LABEL
Date: 20241219

ACTIVE INGREDIENTS: LIDOCAINE 5 g/100 g
INACTIVE INGREDIENTS: ALPHA-TOCOPHEROL ACETATE; CARBOMER 940; TROLAMINE; GLYCERIN; PROPYLENE GLYCOL; ALCOHOL; CHAMOMILE; CUCUMBER; DISODIUM COCOAMPHODIPROPIONATE; WATER; EDETATE DISODIUM; ALOE VERA LEAF

DCH Numbing Relief Spray, Lidocaine 5%

ACTIVE INGREDIENT

Lidocaine 5%

PURPOSE

Topical anesthetic

INDICATIONS AND USAGE

For the local itching and pain associated with anorectal disorders or inflammation.

WARNINGS

For external use only. Flammable--Keep away from fire or flame.

When using this product avoid contact with eyes, do not exceed recommended dosage unless directed by a doctor, do not put this product into the rectum by using fingers or any mechanical device or applicator, contents under pressure. Do not puncture or incinerate. Do not store at temperatures above 120F.

Stop use and ask a doctor if rectal bleeding occurs, condition worsens or does not improve within 7 days, allergic reaction occurs to ingredients in this product, symptom being treated does not subside or if redness, irritation, swelling, pain or other symptoms develop or increase. i

KEEP OUT OF REACH OF CHILDREN

If swallowed, get medical help or contact a Poison Control Center right away.

DOSAGE AND ADMINISTRATION

When practical, cleanse the affected area with mild soap and warm water, Rinse thoroughly and gently pat dry. Spray affected area. Wash hands after applying. Adults and children 2 years of age and older, apply externally to the affected area up to 6 times a day. Children under 12 years of age: consult a doctor.

INACTIVE INGREDIENT

Water, alcohol denat., propylene glycol, glycerin, aloe barbadensis leaf extract, tocopheryl acetate, chamomilla recutita (matricaria) flower extract, cucumis sativus (cucumber) fruit extract, disodium cocoamphodipropionate, carbomer, disodium EDTA, triethanolamine.